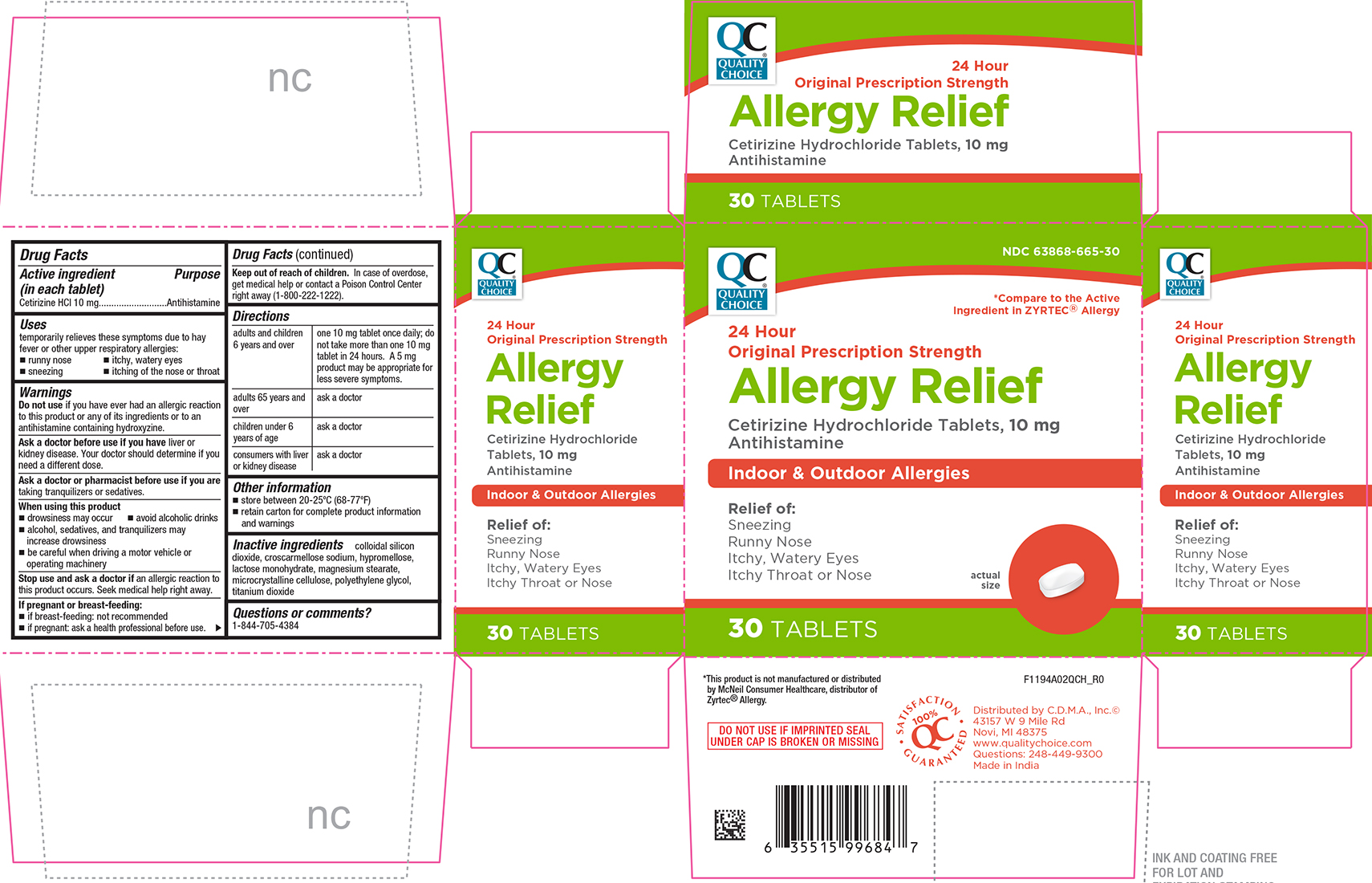 DRUG LABEL: Allergy Relief
NDC: 63868-665 | Form: TABLET, COATED
Manufacturer: CHAIN DRUG MARKETING ASSOCIATION INC.
Category: otc | Type: HUMAN OTC DRUG LABEL
Date: 20241011

ACTIVE INGREDIENTS: CETIRIZINE HYDROCHLORIDE 10 mg/1 1
INACTIVE INGREDIENTS: LACTOSE MONOHYDRATE; CROSCARMELLOSE SODIUM; SILICON DIOXIDE; MAGNESIUM STEARATE; CELLULOSE, MICROCRYSTALLINE; HYPROMELLOSE, UNSPECIFIED; TITANIUM DIOXIDE; POLYETHYLENE GLYCOL, UNSPECIFIED

QCH - 1194A - 2019-1007

Cetirizine Hydrochloride Tablets

Drug Facts

Active ingredient (in each tablet)

Cetirizine HCl 10 mg

Purpose

Antihistamine

Uses

temporarily relieves these symptoms due to hay fever or other upper respiratory allergies:

- runny nose
- sneezing
- itchy, watery eyes
- itching of the nose or throat

Do not use

if you have ever had an allergic reaction to this product or any of its ingredients or to an antihistamine containing hydroxyzine.

Ask a doctor befor use if you have

liver or kidney disease. Your doctor should determine if you need a different dose.

Ask a doctor or pharmacist before use if you are

taking tranquilizers or sedatives.

WHEN USING THIS PRODUCT

- drowsiness may occur
- avoid alcoholic drinks
- alcohol, sedatives, and tranquilizers may increase drowsiness
- be careful when driving a motor vehicle or operating machinery

Stop use and ask a doctor if

an allergic reaction to this product occurs. Seek medical help right away.

If pregnant or breast-feeding:

- if breast-feeding: not recommended
- if pregnant: ask a health professional before use.

Keep out of reach of children.

In case of overdose, get medical help or contact a Poison Control Center right away (1-800-222-1222).

DIRECTIONS

adults and children 6 years and over | one 10 mg tablet once daily; do not take more than one 10 mg tablet in 24 hours. A 5 mg product may be appropriate for less severe symptoms.
adults 65 years and over | ask a doctor
children under 6 years of age | ask a doctor
consumers with liver or kidney disease | ask a doctor

Other information

- store between 20 to 25°C (68 to 77°F)
- retain carton for complete product information and warnings

Inactive ingredients

colloidal silicon dioxide, croscarmellose sodium, hypromellose, lactose monohydrate, magnesium stearate, microcrystalline cellulose, polyethylene glycol, titanium dioxide.

Questions or comments?

1-844-705-4384

PRINCIPAL DISPLAY PANEL

Quality Choice®

NDC 63868-665-30

*Compare to the Active Ingredient in ZYRTEC® Allergy

24 Hour

Original Prescription Strength

Allergy Relief

Cetirizine Hydrochloride Tablets 10 mg | Antihistamine

Indoor & Outdoor Allergies

Relief of:

Sneezing

Runny Nose

Itchy, Watery Eyes

Itchy Throat or Nose

30 Tablets